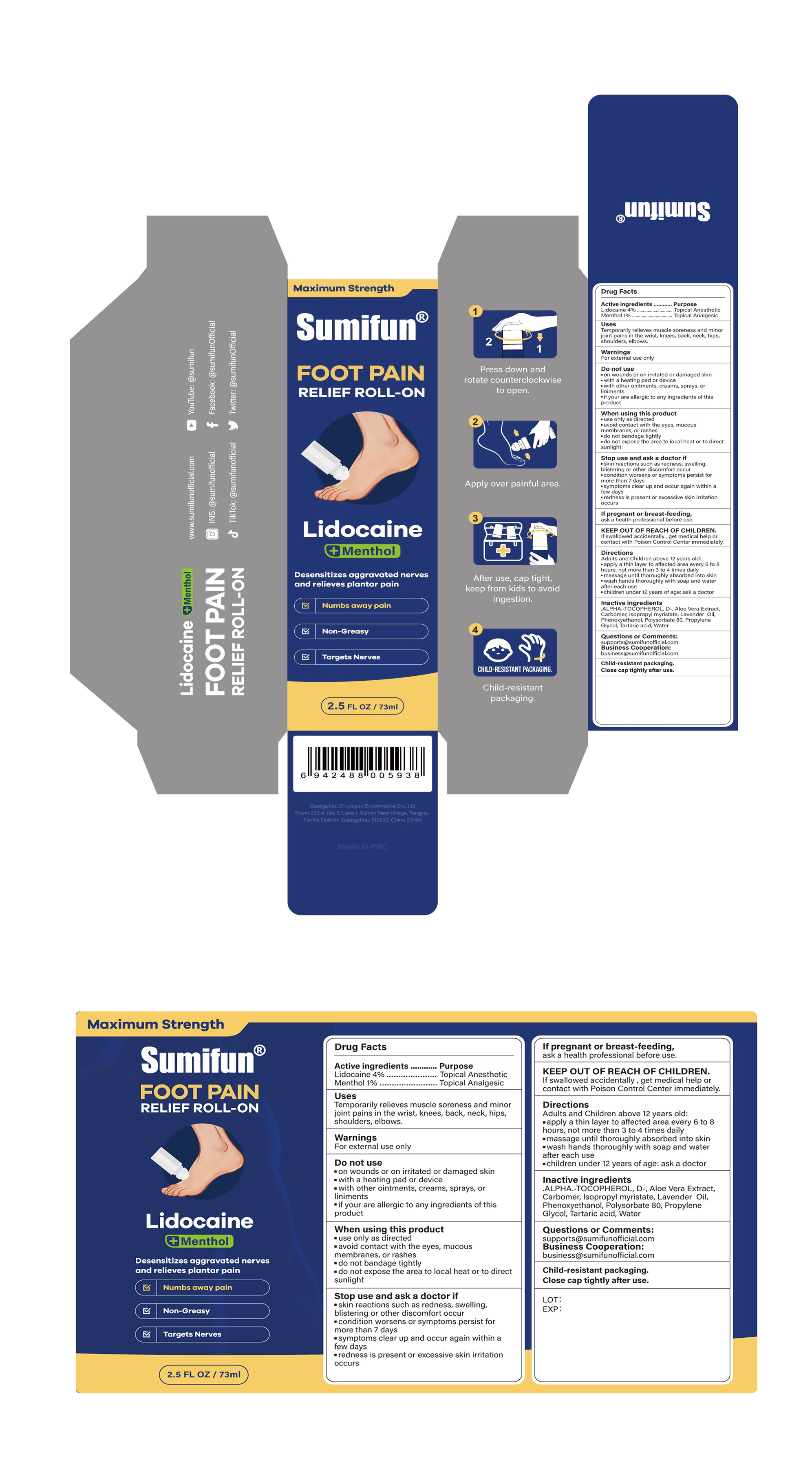 DRUG LABEL: FOOT PAIN RELIEF ROLL-ON
NDC: 84165-017 | Form: LIQUID
Manufacturer: Guangzhou Zhupuyou E-commerce Co., Ltd
Category: otc | Type: HUMAN OTC DRUG LABEL
Date: 20251119

ACTIVE INGREDIENTS: LIDOCAINE 4 g/100 mL; MENTHOL 1 g/100 mL
INACTIVE INGREDIENTS: .ALPHA.-TOCOPHEROL, D-; LAVENDER OIL; PHENOXYETHANOL; CARBOMER; TARTARIC ACID; ALOE VERA LEAF; ISOPROPYL MYRISTATE; POLYSORBATE 80; PROPYLENE GLYCOL; WATER

84165-017 FOOT PAIN RELIEF ROLL-ON

ACTIVE INGREDIENT

Lidocaine 4%
Menthol 1%

PURPOSE

Topical Analgesic

INDICATIONS AND USAGE

Temporarily relieves muscle soreness and minorjoint pains in the wrist, knees, back, neck, hipsshoulders,elbows.

WARNINGS

For external use only

DO NOT USE

on wounds or on irritated or damaged skin

with a heating pad or device

with other ointments, creams, sprays, or liniments
if your are allergic to any ingredients of thisproduct

WHEN USING

use only as directed
avoid contact with the eyes, mucousmembranes, or rashes
do not bandage tightly
do not expose the area to local heat or to direct sunlight

STOP USE

skin reactions such as redness, swelling,blistering or other discomfort occur
condition worsens or symptoms persist formore than 7 days
symptoms clear up and occur again within afew days
redness is present or excessive skin irritation occurs

KEEP OUT OF REACH OF CHILDREN

If swallowed accidentally , get medical help or contact with Poison Control Center immediately.

DOSAGE AND ADMINISTRATION

Adults and Children above 12 years old:
apply a thin layer to affected area every 6 to 8 hours, not more than 3 to 4 times daily
massage until thoroughly absorbed into skin
wash hands thoroughly with soap and water after each use
children under 12 years of age: ask a doctor

INACTIVE INGREDIENT

.ALPHA.-TOCOPHEROL, D-
Aloe Vera Extract
Carbomer
Isopropyl myristate
Lavender Oil
Phenoxyethanol
Polysorbate 80
Propylene Glycol
Tartaric acid
Water